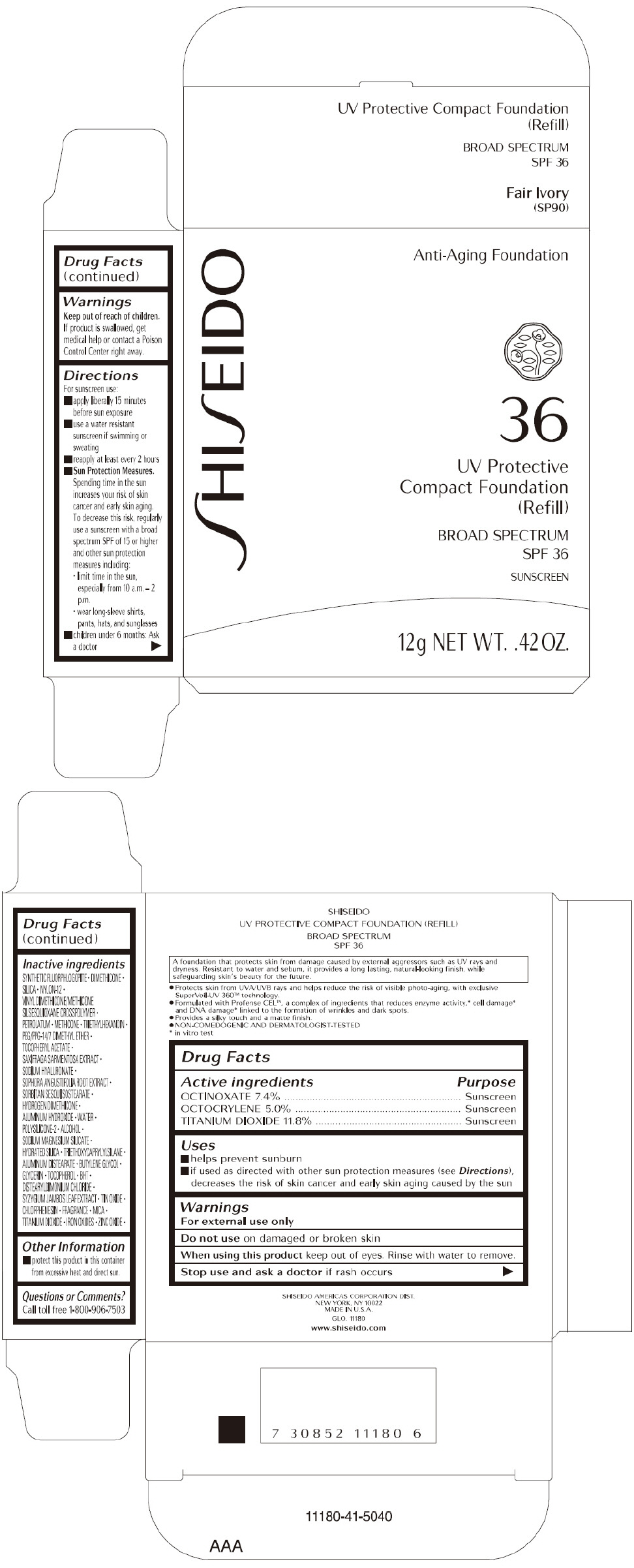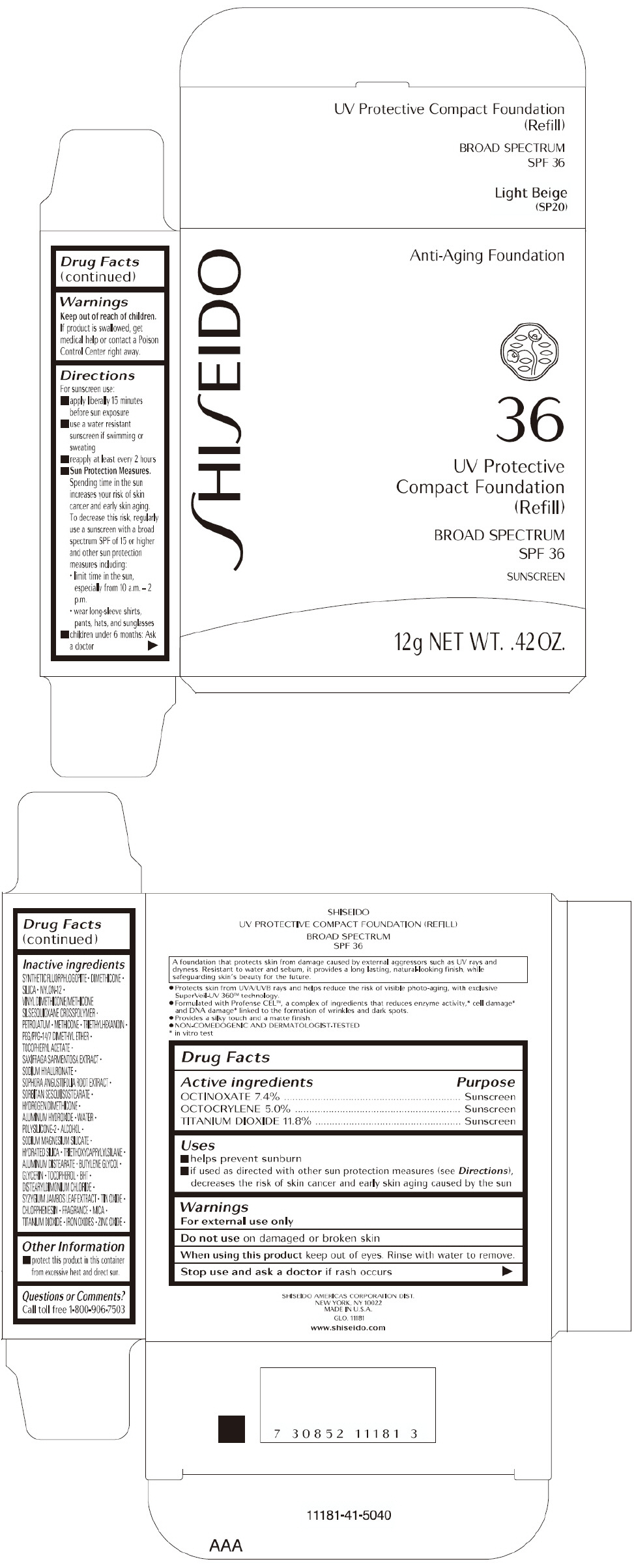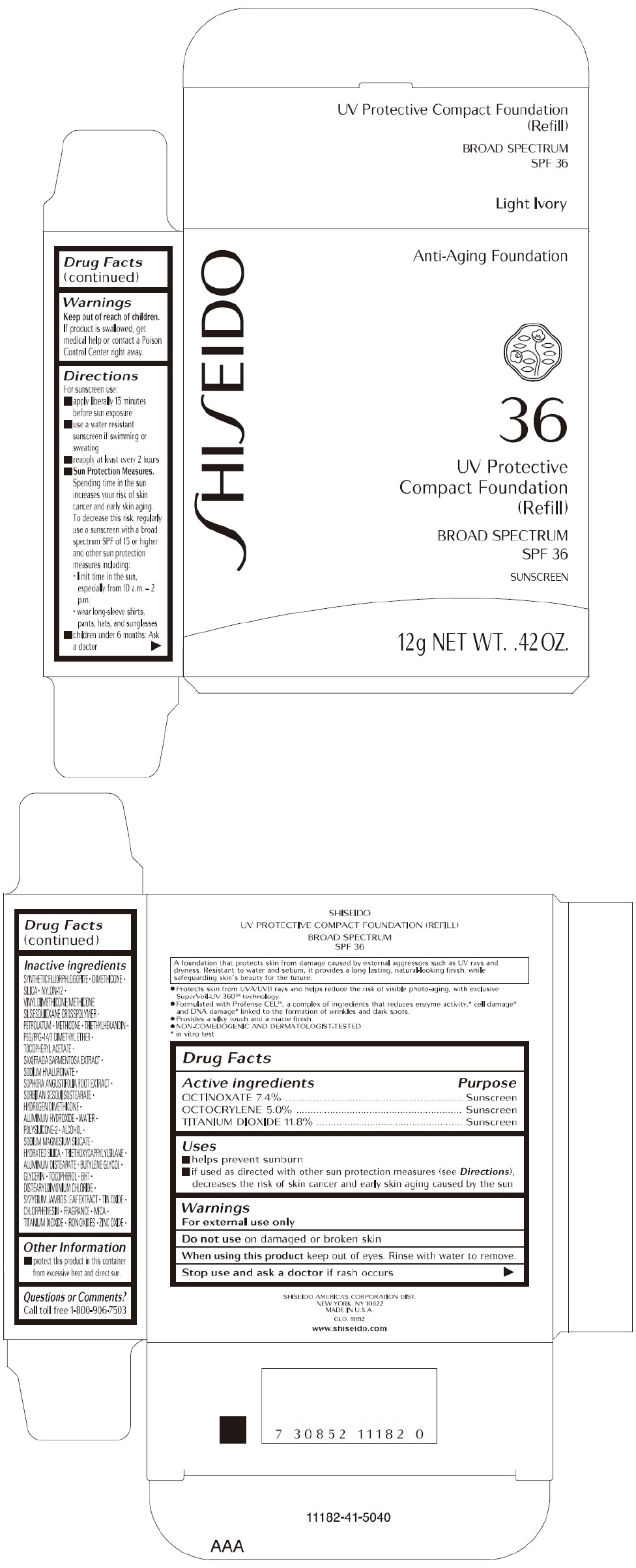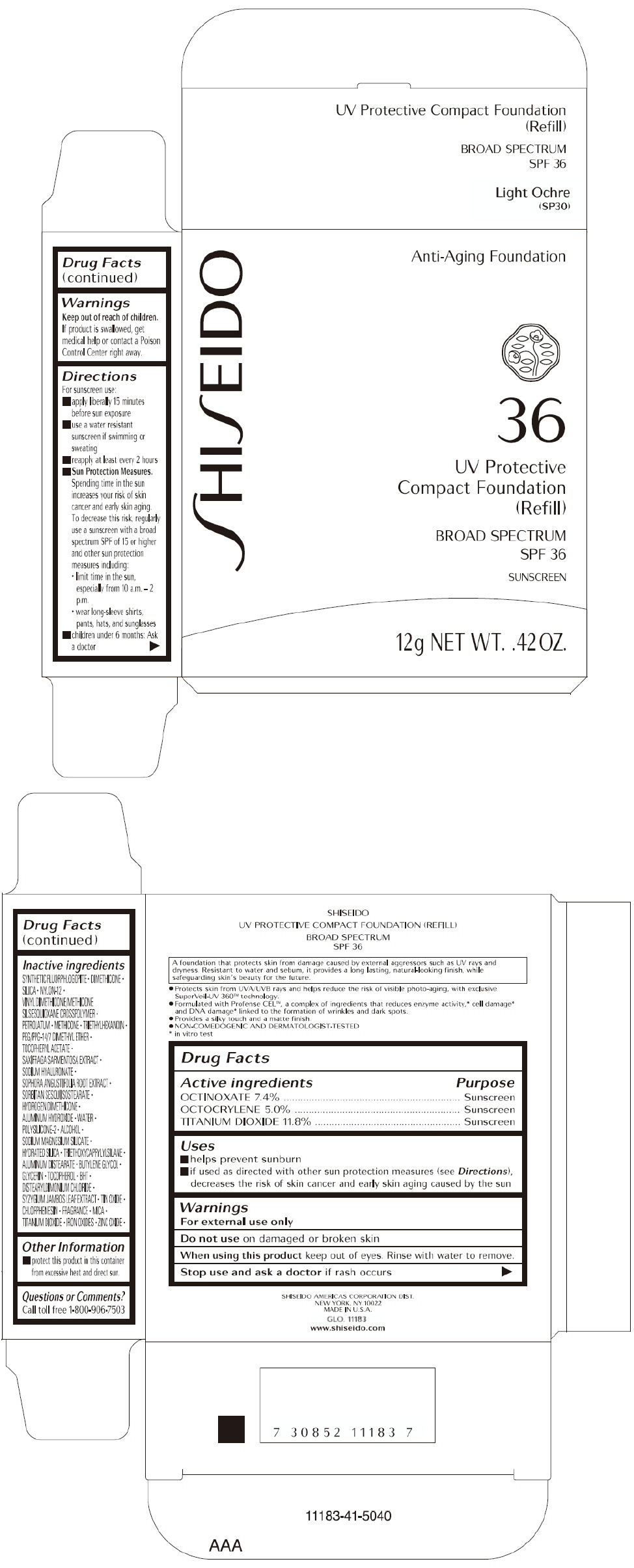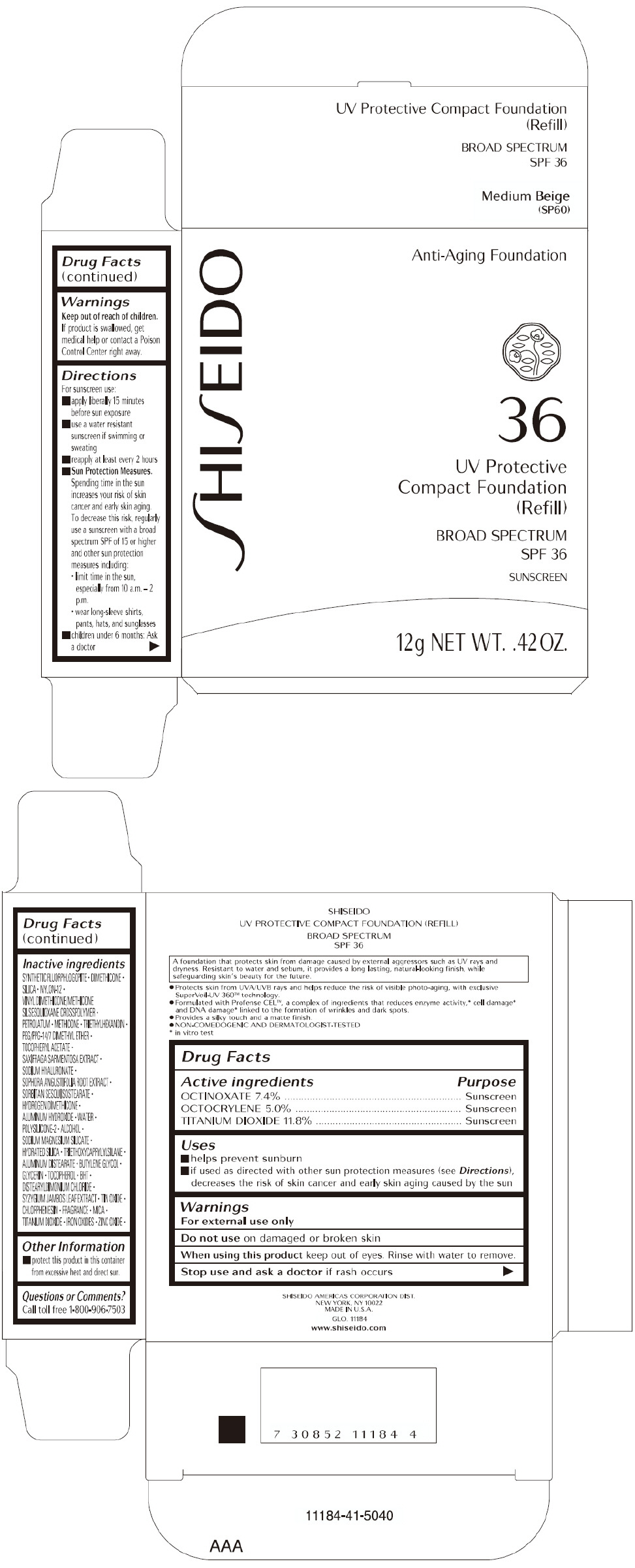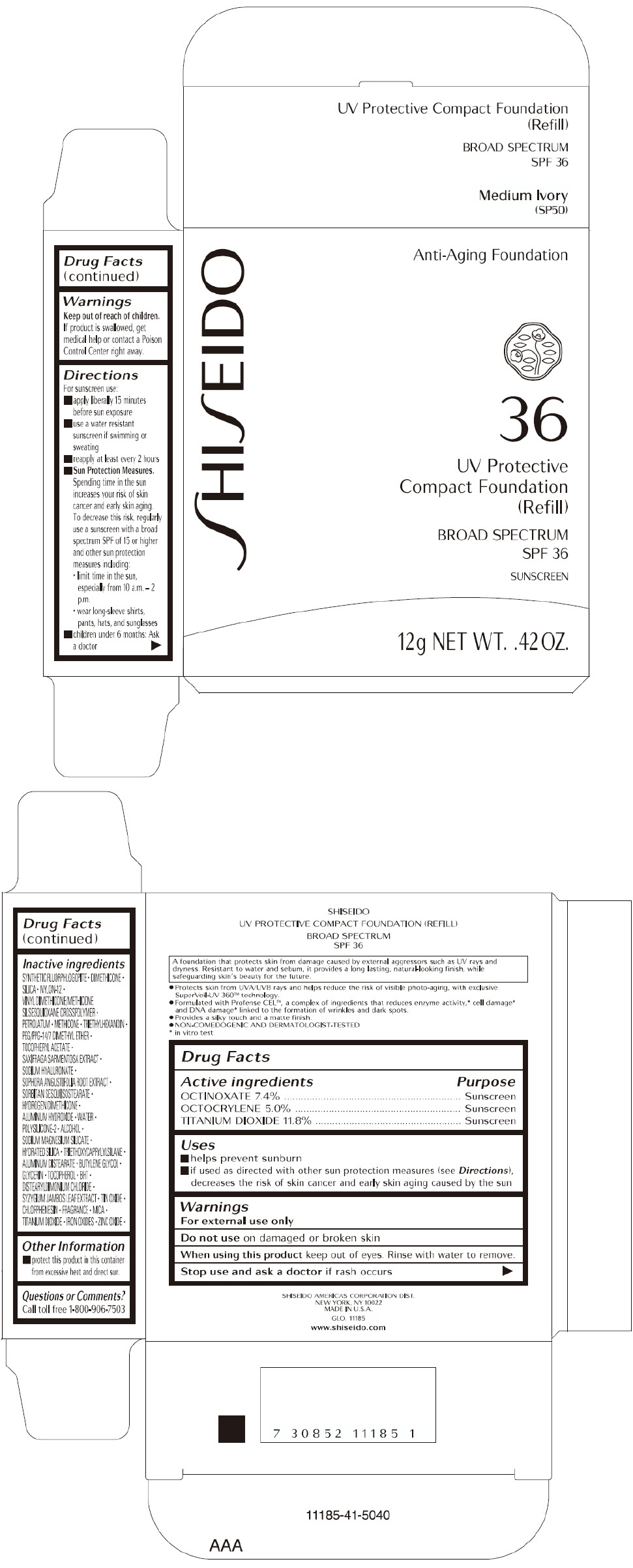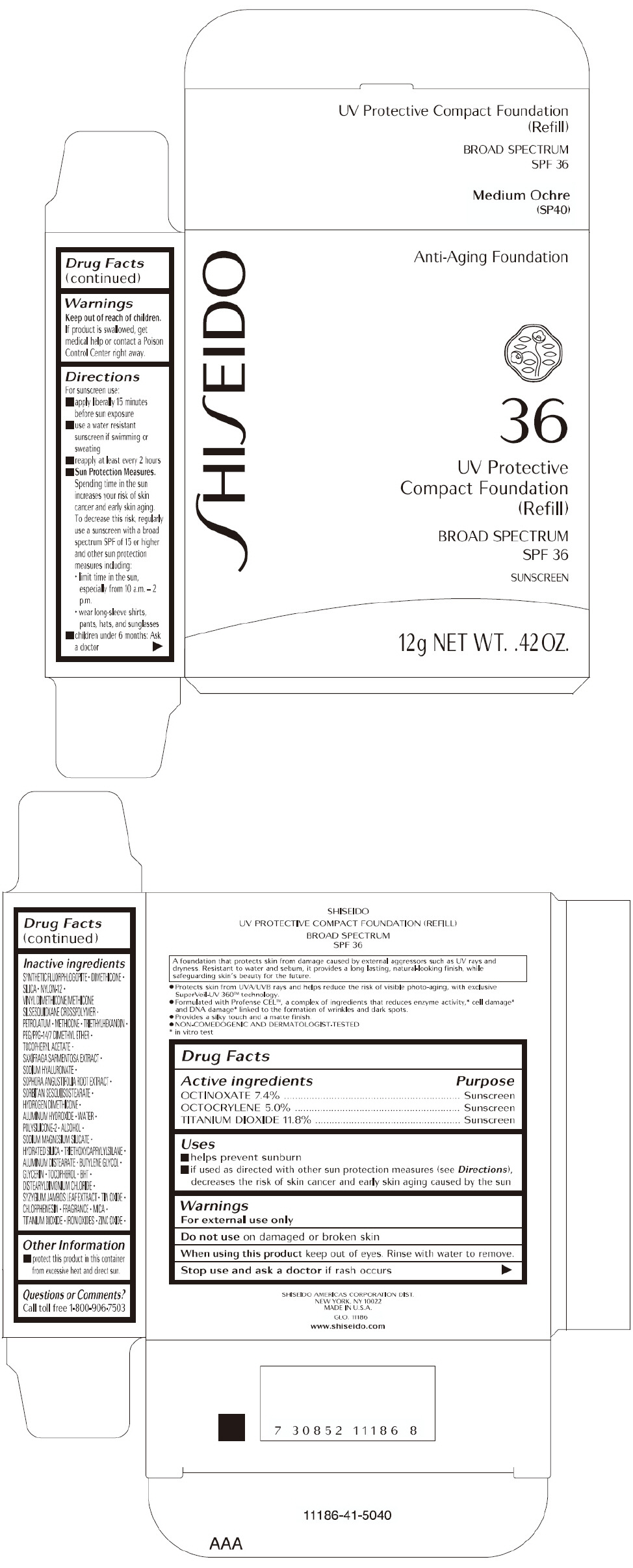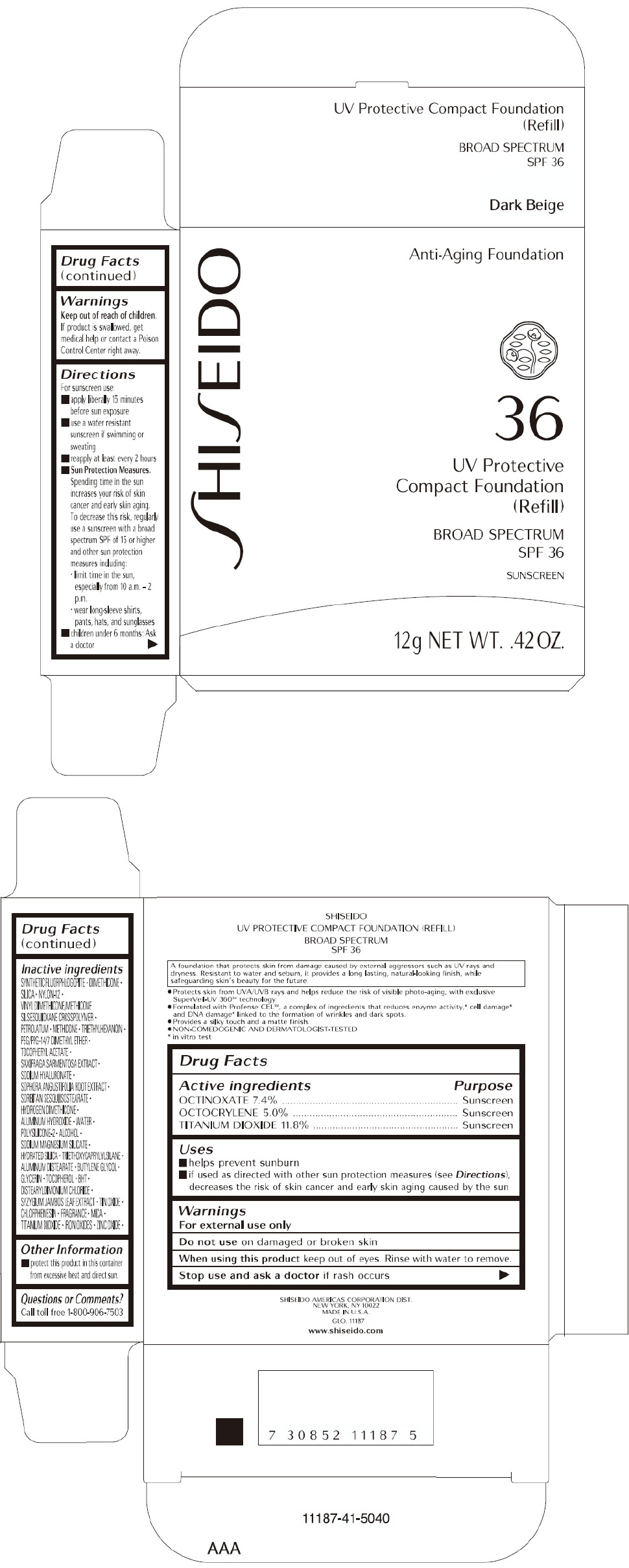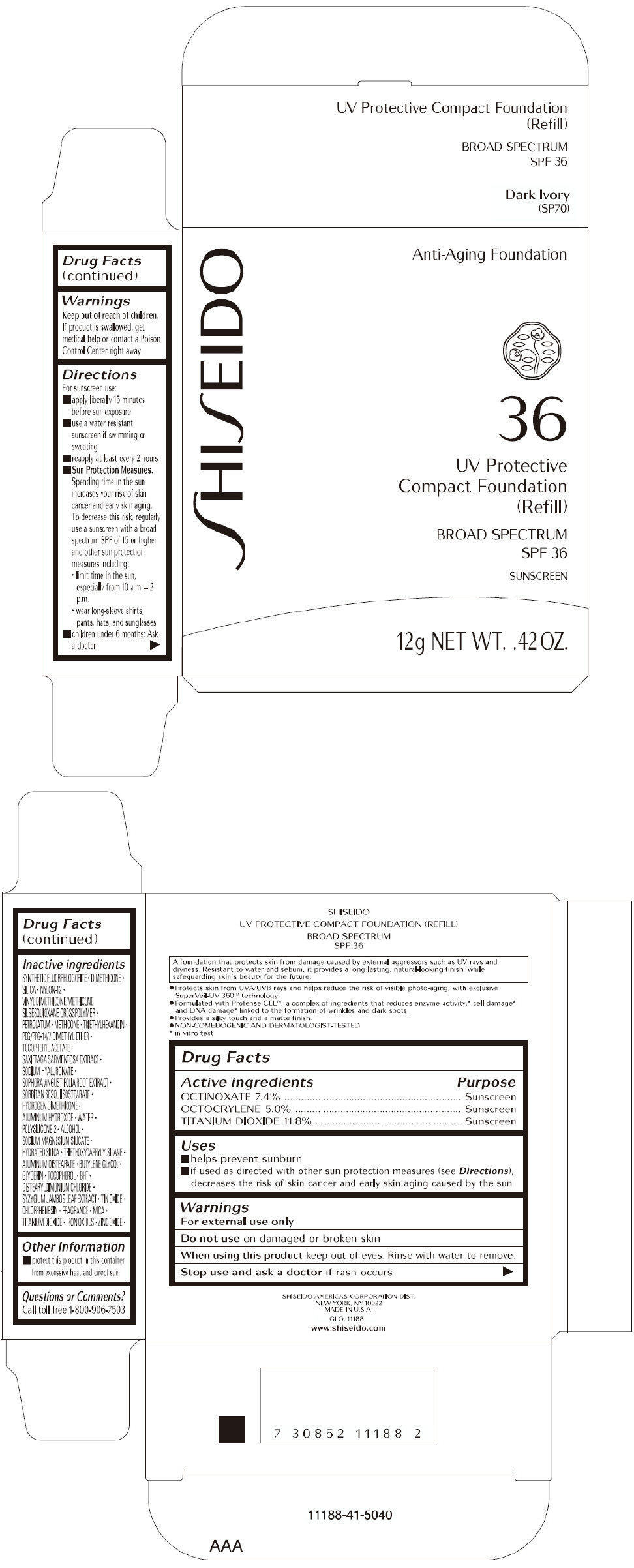 DRUG LABEL: SHISEIDO UV PROTECTIVE COMPACT (REFILL)
NDC: 58411-122 | Form: POWDER
Manufacturer: SHISEIDO AMERICAS CORPORATION
Category: otc | Type: HUMAN OTC DRUG LABEL
Date: 20260225

ACTIVE INGREDIENTS: OCTINOXATE 888 mg/12 g; OCTOCRYLENE 600 mg/12 g; TITANIUM DIOXIDE 1416 mg/12 g
INACTIVE INGREDIENTS: DIMETHICONE; SILICON DIOXIDE; NYLON-12; PETROLATUM; METHICONE (20 CST); TRIETHYLHEXANOIN; PEG/PPG-14/7 DIMETHYL ETHER; .ALPHA.-TOCOPHEROL ACETATE, DL-; SAXIFRAGA STOLONIFERA LEAF; HYALURONATE SODIUM; SOPHORA FLAVESCENS ROOT; ALUMINUM HYDROXIDE; WATER; ALCOHOL; HYDRATED SILICA; TRIETHOXYCAPRYLYLSILANE; ALUMINUM DISTEARATE; BUTYLENE GLYCOL; GLYCERIN; .ALPHA.-TOCOPHEROL; BUTYLATED HYDROXYTOLUENE; DISTEARYLDIMONIUM CHLORIDE; SYZYGIUM JAMBOS LEAF; STANNIC OXIDE; CHLORPHENESIN; MICA; FERRIC OXIDE RED; FERRIC OXIDE YELLOW; FERROSOFERRIC OXIDE; ZINC OXIDE

SHISEIDO UV PROTECTIVE COMPACT (REFILL)

Drug Facts

ACTIVE INGREDIENT

ACTIVE INGREDIENTS: | Purpose
OCTINOXATE 7.4% | Sunscreen
OCTOCRYLENE 5.0% | Sunscreen
TITANIUM DIOXIDE 11.8% | Sunscreen

Uses

- helps prevent sunburn
- if used as directed with other sun protection measures (see Directions), decreases the risk of skin cancer and early skin aging caused by the sun

Warnings

For external use only

Do not useon damaged or broken skin

WHEN USING

When using this productkeep out of eyes. Rinse with water to remove.

Stop use and ask a doctorif rash occurs

Keep out of reach of children.If product is swallowed, get medical help or contact a Poison Control Center right away.

Directions

For sunscreen use:

- apply liberally 15 minutes before sun exposure
- use a water resistant sunscreen if swimming or sweating
- reapply at least every 2 hours
- Sun Protection Measures. Spending time in the sun increases your risk of skin cancer and early skin aging. To decrease this risk, regularly use a sunscreen with a broad spectrum SPF of 15 or higher and other sun protection measures including:
  - limit time in the sun, especially from 10 a.m. – 2 p.m.
  - wear long-sleeve shirts, pants, hats, and sunglasses
- children under 6 months: Ask a doctor

Inactive Ingredients

SYNTHETIC FLUORPHLOGOPITE,DIMETHICONE,SILICA,NYLON-12,VINYL DIMETHICONE/METHICONE SILSESQUIOXANE CROSSPOLYMER,PETROLATUM,METHICONE,TRIETHYLHEXANOIN,PEG/PPG-14/7 DIMETHYL ETHER,TOCOPHERYL ACETATE,SAXIFRAGA SARMENTOSA EXTRACT,SODIUM HYALURONATE,SOPHORA ANGUSTIFOLIA ROOT EXTRACT,SORBITAN SESQUIISOSTEARATE,HYDROGEN DIMETHICONE,ALUMINUM HYDROXIDE,WATER,POLYSILICONE-2,ALCOHOL,SODIUM MAGNESIUM SILICATE,HYDRATED SILICA,TRIETHOXYCAPRYLYLSILANE,ALUMINUM DISTEARATE,BUTYLENE GLYCOL,GLYCERIN,TOCOPHEROL,BHT,DISTEARYLDIMONIUM CHLORIDE,SYZYGIUM JAMBOS LEAF EXTRACT,TIN OXIDE,CHLORPHENESIN,FRAGRANCE,MICA,TITANIUM DIOXIDE,IRON OXIDES,ZINC OXIDE,

Other information

- protect this product in this container from excessive heat and direct sun.

Questions or comments?

Call toll free 1-800-906-7503

PRINCIPAL DISPLAY PANEL - 12 g Tray Carton - Fair Ivory

SHI SEIDO

Anti-Aging Foundation

36

UV Protective
Compact Foundation
(Refill)

BROAD SPECTRUM
SPF 36

SUNSCREEN

12g NET WT. .42 OZ.

PRINCIPAL DISPLAY PANEL - 12 g Tray Carton - Light Beige

SHI SEIDO

Anti-Aging Foundation

36

UV Protective
Compact Foundation
(Refill)

BROAD SPECTRUM
SPF 36

SUNSCREEN

12g NET WT. .42 OZ.

PRINCIPAL DISPLAY PANEL - 12 g Tray Carton - Light Ivory

SHI SEIDO

Anti-Aging Foundation

36

UV Protective
Compact Foundation
(Refill)

BROAD SPECTRUM
SPF 36

SUNSCREEN

12g NET WT. .42 OZ.

PRINCIPAL DISPLAY PANEL - 12 g Tray Carton - Light Ochre

SHI SEIDO

Anti-Aging Foundation

36

UV Protective
Compact Foundation
(Refill)

BROAD SPECTRUM
SPF 36

SUNSCREEN

12g NET WT. .42 OZ.

PRINCIPAL DISPLAY PANEL - 12 g Tray Carton - Medium Beige

SHI SEIDO

Anti-Aging Foundation

36

UV Protective
Compact Foundation
(Refill)

BROAD SPECTRUM
SPF 36

SUNSCREEN

12g NET WT. .42 OZ.

PRINCIPAL DISPLAY PANEL - 12 g Tray Carton - Medium Ivory

SHI SEIDO

Anti-Aging Foundation

36

UV Protective
Compact Foundation
(Refill)

BROAD SPECTRUM
SPF 36

SUNSCREEN

12g NET WT. .42 OZ.

PRINCIPAL DISPLAY PANEL - 12 g Tray Carton - Medium Ochre

SHI SEIDO

Anti-Aging Foundation

36

UV Protective
Compact Foundation
(Refill)

BROAD SPECTRUM
SPF 36

SUNSCREEN

12g NET WT. .42 OZ.

PRINCIPAL DISPLAY PANEL - 12 g Tray Carton - Dark Beige

SHI SEIDO

Anti-Aging Foundation

36

UV Protective
Compact Foundation
(Refill)

BROAD SPECTRUM
SPF 36

SUNSCREEN

12g NET WT. .42 OZ.

PRINCIPAL DISPLAY PANEL - 12 g Tray Carton - Dark Ivory

SHI SEIDO

Anti-Aging Foundation

36

UV Protective
Compact Foundation
(Refill)

BROAD SPECTRUM
SPF 36

SUNSCREEN

12g NET WT. .42 OZ.